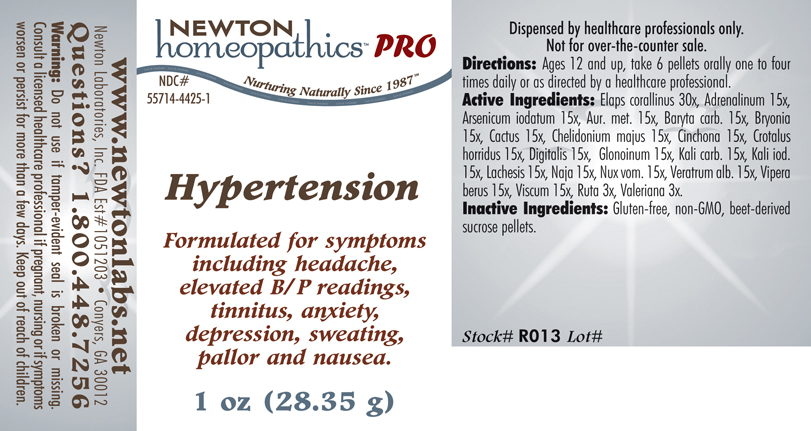 DRUG LABEL: Hypertension 
NDC: 55714-4425 | Form: PELLET
Manufacturer: Newton Laboratories, Inc.
Category: homeopathic | Type: HUMAN PRESCRIPTION DRUG LABEL
Date: 20110601

ACTIVE INGREDIENTS: Micrurus Corallinus Venom 30 [hp_X]/1 g; Epinephrine 15 [hp_X]/1 g; Arsenic Triiodide 15 [hp_X]/1 g; Gold 15 [hp_X]/1 g; Barium Carbonate 15 [hp_X]/1 g; Bryonia Alba Root 15 [hp_X]/1 g; Selenicereus Grandiflorus Stem 15 [hp_X]/1 g; Chelidonium Majus 15 [hp_X]/1 g; Cinchona Officinalis Bark 15 [hp_X]/1 g; Crotalus Horridus Horridus Venom 15 [hp_X]/1 g; Digitalis 15 [hp_X]/1 g; Nitroglycerin 15 [hp_X]/1 g; Potassium Carbonate 15 [hp_X]/1 g; Potassium Iodide 15 [hp_X]/1 g; Lachesis Muta Venom 15 [hp_X]/1 g; Naja Naja Venom 15 [hp_X]/1 g; Strychnos Nux-vomica Seed 15 [hp_X]/1 g; Veratrum Album Root 15 [hp_X]/1 g; Vipera Berus Venom 15 [hp_X]/1 g; Viscum Album Fruiting Top 15 [hp_X]/1 g; Ruta Graveolens Flowering Top 3 [hp_X]/1 g; Valerian 3 [hp_X]/1 g
INACTIVE INGREDIENTS: Sucrose

Hypertension

INDICATIONS & USAGE SECTION

HYPERTENSION Formulated for symptoms including headache, elevated B/P readings, tinnitus, anxiety, depression, sweating, pallor and nausea.

DOSAGE & ADMINISTRATION SECTION

Directions: Ages 12 and up, take 6 pellets orally one to four times daily or as directed by a healthcare professional.

ACTIVE INGREDIENT SECTION

Elaps corallinus 30x, Adrenalinum 15x, Arsenicum iodatum 15x, Aur. met. 15x, Baryta carb. 15x, Bryonia 15x, Cactus 15x, Chelidonium majus 15x, Cinchona 15x, Crotalus horridus 15x, Digitalis 15x, Glonoinum 15x, Kali carb. 15x, Kali iod. 15x, Lachesis 15x, Naja 15x, Nux vom. 15x, Veratrum alb. 15x, Vipera berus 15x, Viscum 15x, Ruta 3x, Valeriana 3x.

PURPOSE SECTION

Formulated for symptoms including headache, elevated B/P readings, tinnitus, anxiety, depression, sweating, pallor and nausea.

INACTIVE INGREDIENT SECTION

Inactive Ingredients: Gluten-free, non-GMO, beet-derived sucrose pellets.

QUESTIONS? SECTION

www.newtonlabs.net Newton Laboratories, Inc. FDA Est # 1051203 - Conyers, GA 30012
Questions? 1.800.448.7256

WARNINGS SECTION

Warning: Do not use if tamper - evident seal is broken or missing. Consult a licensed healthcare professional if pregnant, nursing or if symptoms worsen or persist for more than a few days. Keep out of reach of children.

PREGNANCY OR BREAST FEEDING SECTION

Consult a licensed healthcare professional if pregnant or nursing or if symptoms worsen or persist for more than a few days.

KEEP OUT OF REACH OF CHILDREN SECTION

Keep out of reach of children.